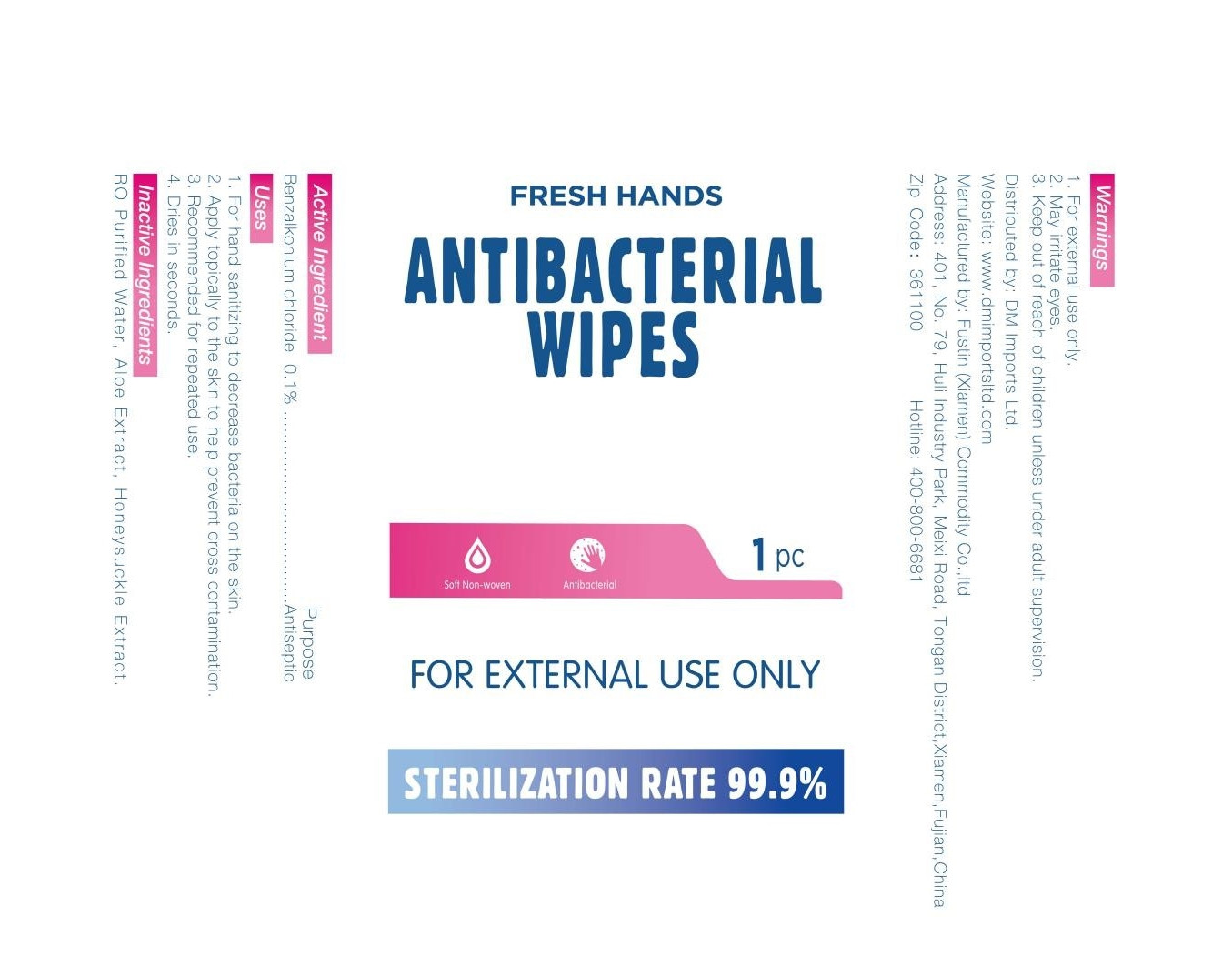 DRUG LABEL: ANTIBACTERIAL WIPES
NDC: 42129-009 | Form: CLOTH
Manufacturer: Fustin (Xiamen) Commodity Co., Ltd.
Category: otc | Type: HUMAN OTC DRUG LABEL
Date: 20200526

ACTIVE INGREDIENTS: BENZALKONIUM CHLORIDE 0.00425 g/1 1
INACTIVE INGREDIENTS: ALOE VERA LEAF; LONICERA CAPRIFOLIUM FLOWER; WATER

DOSAGE AND ADMINISTRATION

Store in a cool and dry place

INACTIVE INGREDIENT

RO Purified Water,Aloe Vera Extract ,Honeysuckle Extract

INDICATIONS AND USAGE

1. For hand sanitizing to decrease bacteria on the skin.
2. Apply topically to the skin to help prevent cross contamination.
3. Recommended for repeated use.
4. Dries in seconds.

ACTIVE INGREDIENT

Benzalkonium Chloride

keep out of reach of children

PURPOSE

Disinfection
Sterilization
No Rinseing

WARNINGS

1. For external use only.
2. May rritate eyes.
3. Keep out of reach of children unless under adult supervision.